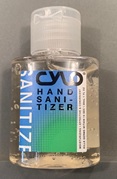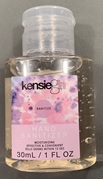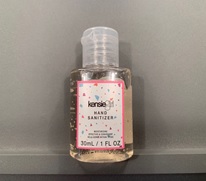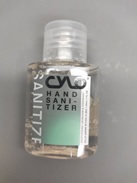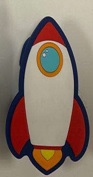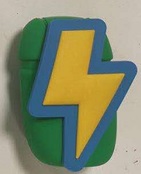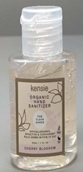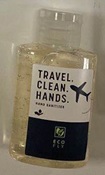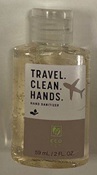 DRUG LABEL: Hand Sanitizer
NDC: 78445-301 | Form: GEL
Manufacturer: Guangzhou Kangfei Cosmetics Co., Ltd.
Category: otc | Type: HUMAN OTC DRUG LABEL
Date: 20210830

ACTIVE INGREDIENTS: BENZALKONIUM CHLORIDE 0.1 g/100 mL
INACTIVE INGREDIENTS: TROLAMINE; POLYOXYL 40 HYDROGENATED CASTOR OIL; CARBOMER INTERPOLYMER TYPE A (ALLYL SUCROSE CROSSLINKED); WATER

Hand Sanitizer

Hand Sanitizer

Active Ingredient(s)

Benzalkonium chloride 0.1g/100ml. Purpose: Antiseptic

Purpose

Antiseptic, Hand Sanitizer

Use

Hand Sanitizer to help reduce bacteria that potentially can cause disease. For use when soap and water are not available.

Warnings

For external use only. Flammable. Keep away from heat or flame

Do not use

- in children less than 2 months of age
- on open skin wounds

When using this product keep out of eyes, ears, and mouth. In case of contact with eyes, rinse eyes thoroughly with water.
Stop use and ask a doctor if irritation or rash occurs. These may be signs of a serious condition.
Keep out of reach of children. If swallowed, get medical help or contact a Poison Control Center right away.

Stop use and ask a doctor if irritation or rash occurs. These may be signs of a serious condition.

Keep out of reach of children. If swallowed, get medical help or contact a Poison Control Center right away.

Directions

- Place enough product on hands to cover all surfaces. Rub hands together until dry.
- Supervise children under 6 years of age when using this product to avoid swallowing.

Other information

- Store between 15-30C (59-86F)
- Avoid freezing and excessive heat above 40C (104F)

Inactive ingredients

WATER
PEG-40 HYDROGENATED CASTOR OIL
ACRYLATES/C10-30 ALKYL ACRYLATE CROSSPOLYMER
TRIETHANOLAMINE